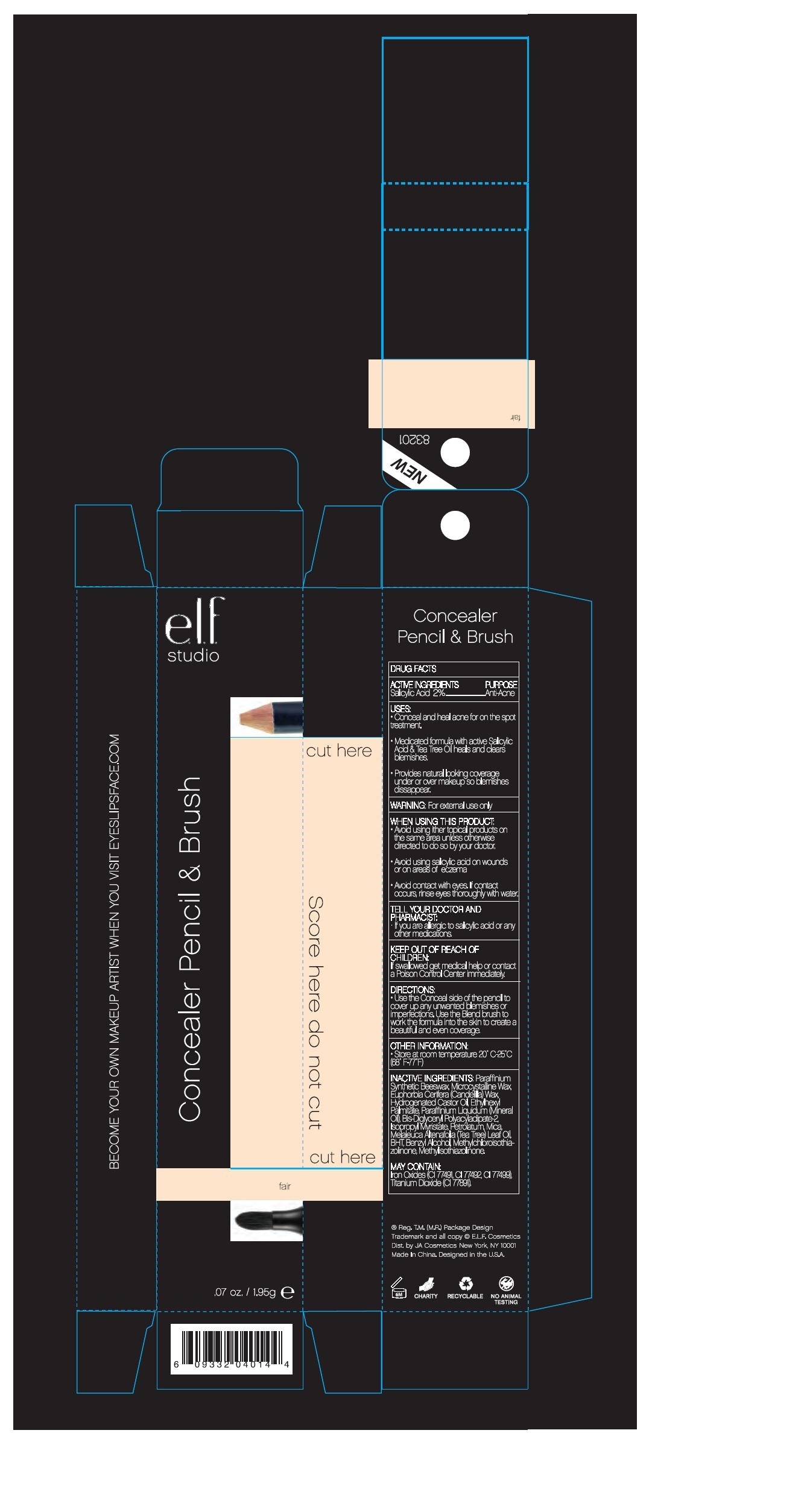 DRUG LABEL: ELF Conceler Pencil and Brush
NDC: 52664-009 | Form: PASTE
Manufacturer: Hangzhou Facecare Cosmetics Co., Ltd.
Category: otc | Type: HUMAN OTC DRUG LABEL
Date: 20101118

ACTIVE INGREDIENTS: SALICYLIC ACID 2.0 g/100 g
INACTIVE INGREDIENTS: YELLOW WAX 15 g/100 g; MICROCRYSTALLINE WAX; CANDELILLA WAX; TEA TREE OIL; ETHYLHEXYL PALMITATE; MINERAL OIL; CAMPHOR OIL; ISOPROPYL MYRISTATE; PETROLATUM; MICA; BUTYLATED HYDROXYTOLUENE; BENZYL ALCOHOL; METHYLCHLOROISOTHIAZOLINONE; METHYLISOTHIAZOLINONE; FERRIC OXIDE RED; FERRIC OXIDE YELLOW; FERROSOFERRIC OXIDE; TITANIUM DIOXIDE

Drug Fact

Active Ingredient:

Salicylic Acid 2.0%

Purpose:

Anti-Acne

Uses:

- Conceal and heal acn for on the spot treatment
- Medicated formula with active salicylic acid and tea tree oil heels and clears blemishes
- Provides natural looking coverage under or above makeup so blemishes disappear

Warning:

For external use only

When Using This Product:

Avoid using other topical products on the same area unless otherwise directed by your doctor

Avoid using salicylic acid on wounds or on areas of eczema

Avoid contact with eyes. If contact occurs, rinse eyes thoroughly with water

Tell Your Doctor And Pharmacist If

You are allergic to salicylic acid or any other medications

Keep Out of Reach of Children:

If swallowed get medical help or contact a Poison Control Center immediately

Directions:

Use the conceal side of the pencil to cover up any unwanted blemishes and imperfections. Use the blend brush to work the formula into the skin to create a beautiful and even coverage.

Other Information:

Store at room temperature 20-25C (68-77F)

Inactive Ingredient:

Synthetic Beeswax, Microstalline Wax, Euphorbia Cerifera (Candelilla) Wax, Hydrogenated Castor Oil, Ethylhexy Palmitate, Paraffinium Liquidum (Mineral Oil), Bis-Diglyceryl Polyacyladipate-2, Isopropyl Myristate, Petrolatum, Mica, Melaleuca Alternafolia (Tea Tree) Leaf Oil, BHT, Benzyl Alcohol, Methylchloroisothiazolinone, Methylisothiazolinone.
May Contain:
Iron Oxide (CI77491, CI77492, CI77499), Titanium Dioxide

PACKAGE LABEL

lab